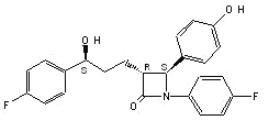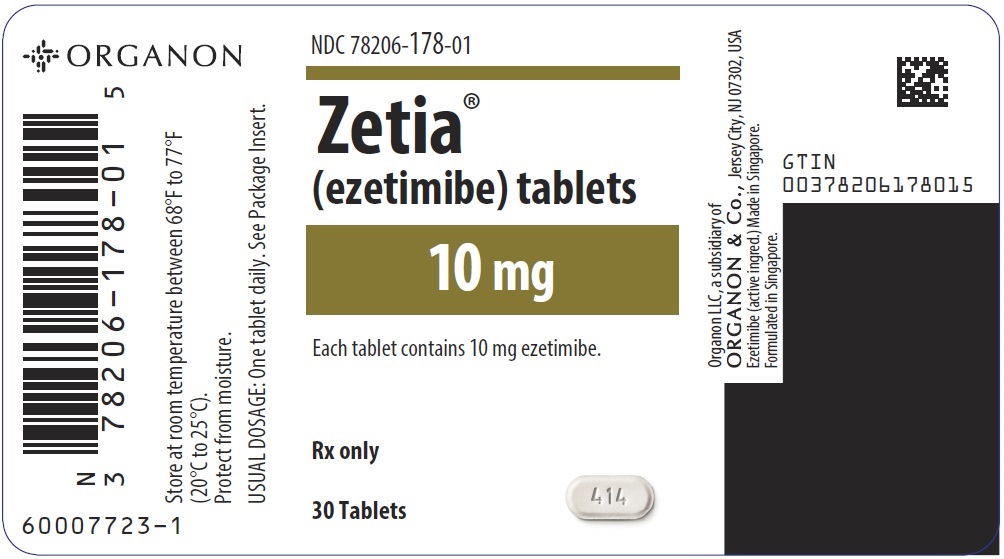 DRUG LABEL: Zetia
NDC: 78206-178 | Form: TABLET
Manufacturer: Organon LLC
Category: prescription | Type: HUMAN PRESCRIPTION DRUG LABEL
Date: 20251125

ACTIVE INGREDIENTS: EZETIMIBE 10 mg/1 1
INACTIVE INGREDIENTS: CROSCARMELLOSE SODIUM; LACTOSE MONOHYDRATE; MAGNESIUM STEARATE; MICROCRYSTALLINE CELLULOSE; POVIDONE, UNSPECIFIED; SODIUM LAURYL SULFATE

HIGHLIGHTS OF PRESCRIBING INFORMATION

These highlights do not include all the information needed to use ZETIA safely and effectively. See full prescribing information for ZETIA.
ZETIA® (ezetimibe) tablets, for oral use
Initial U.S. Approval: 2002

RECENT MAJOR CHANGES

Indications and Usage (1) | 7/2023
Dosage and Administration (2) | 7/2023
Contraindications (4) | 7/2023
Warnings and Precautions (5.1, 5.2, 5.3) | 7/2023

1 INDICATIONS AND USAGE

ZETIA is indicated (1):

- In combination with a statin, or alone when additional low density lipoprotein cholesterol (LDL-C) lowering therapy is not possible, as an adjunct to diet to reduce elevated LDL-C in adults with primary hyperlipidemia, including heterozygous familial hypercholesterolemia (HeFH).
- In combination with a statin as an adjunct to diet to reduce elevated LDL-C in pediatric patients 10 years of age and older with HeFH.
- In combination with fenofibrate as an adjunct to diet to reduce elevated LDL-C in adults with mixed hyperlipidemia.
- In combination with a statin, and other LDL-C lowering therapies, to reduce elevated LDL-C levels in adults and in pediatric patients 10 years of age and older with homozygous familial hypercholesterolemia (HoFH).
- As an adjunct to diet for the reduction of elevated sitosterol and campesterol levels in adults and in pediatric patients 9 years of age and older with homozygous familial sitosterolemia.

When ZETIA is used in combination with a statin, fenofibrate, or other LDL-C lowering therapies, refer to the Prescribing Information of these products for information on the safe and effective use (1).

2 DOSAGE AND ADMINISTRATION

- 10-mg orally once daily, with or without food (2)
- Administer ZETIA either ≥2 hours before or ≥4 hours after administration of a bile acid sequestrant. (2)
- Assess LDL-C when clinically appropriate, as early as 4 weeks after initiating ZETIA. (2)

3 DOSAGE FORMS AND STRENGTHS

- Tablets: 10 mg (3)

4 CONTRAINDICATIONS

- Hypersensitivity to ezetimibe or any excipient of ZETIA. (4)
- When used in combination with a statin, fenofibrate, or other LDL-C lowering therapy, ZETIA is contraindicated in patients for whom a statin, fenofibrate, or other LDL-C lowering therapy are contraindicated. Refer to the Prescribing Information of these products for a list of their contraindications. (4)

5 WARNINGS AND PRECAUTIONS

- Risks Associated with Combination Treatment with a Statin, Fenofibrate, or Other LDL-C Lowering Therapies: Refer to the Prescribing Information of these products for a description of their risks including, but not limited to, the warnings and precautions. (5.1)
- Liver Enzyme Abnormalities and Monitoring: Increases in serum transaminases have been reported with use of ZETIA. Perform liver enzyme testing as clinically indicated and consider withdrawal of ZETIA if increases in ALT or AST ≥3 × ULN persist. (5.2)
- Skeletal Muscle Effects (e.g., Myopathy and Rhabdomyolysis): ZETIA may cause myopathy and rhabdomyolysis. In post-marketing reports, most patients who developed rhabdomyolysis were taking a statin or other agents known to be associated with an increased risk of rhabdomyolysis, such as fibrates. If myopathy is suspected, discontinue ZETIA and other concomitant medications, as appropriate. (5.3)

6 ADVERSE REACTIONS

- Common adverse reactions in clinical trials:
  - ZETIA administered alone (incidence ≥2% and greater than placebo): upper respiratory tract infection, diarrhea, arthralgia, sinusitis, pain in extremity, fatigue, and influenza. (6.1)
  - ZETIA coadministered with a statin (incidence ≥2% and greater than statin alone): nasopharyngitis, myalgia, upper respiratory tract infection, arthralgia, diarrhea, back pain, influenza, pain in extremity, and fatigue. (6.1)

To report SUSPECTED ADVERSE REACTIONS, contact Organon LLC, a subsidiary of Organon & Co., at 1-844-674-3200 or FDA at 1-800-FDA-1088 or www.fda.gov/medwatch.

7 DRUG INTERACTIONS

- Cyclosporine: Combination increases exposure of ZETIA and cyclosporine. Cyclosporine concentrations should be monitored in patients taking ZETIA concomitantly. (7)
- Fibrates: Coadministration of ZETIA with fibrates other than fenofibrate is not recommended until use in patients is adequately studied. If cholelithiasis is suspected in a patient receiving ZETIA and fenofibrate, gallbladder studies are indicated, and alternative lipid-lowering therapy should be considered. (7)
- Bile Acid Sequestrants: Cholestyramine combination decreases exposure of ZETIA. (7)

FULL PRESCRIBING INFORMATION

1 INDICATIONS AND USAGE

ZETIA® is indicated:

- In combination with a statin, or alone when additional low-density lipoprotein cholesterol (LDL-C) lowering therapy is not possible, as an adjunct to diet to reduce elevated LDL-C in adults with primary hyperlipidemia, including heterozygous familial hypercholesterolemia (HeFH).
- In combination with a statin as an adjunct to diet to reduce elevated LDL-C in pediatric patients 10 years of age and older with HeFH.
- In combination with fenofibrate as an adjunct to diet to reduce elevated LDL-C in adults with mixed hyperlipidemia.
- In combination with a statin, and other LDL-C lowering therapies, to reduce elevated LDL-C levels in adults and in pediatric patients 10 years of age and older with homozygous familial hypercholesterolemia (HoFH).
- As an adjunct to diet for the reduction of elevated sitosterol and campesterol levels in adults and in pediatric patients 9 years of age and older with homozygous familial sitosterolemia.

When ZETIA is used in combination with a statin, fenofibrate, or other LDL-C lowering therapies, refer to the Prescribing Information of these products for information on the safe and effective use.

2 DOSAGE AND ADMINISTRATION

- The recommended dose of ZETIA is 10 mg orally once daily, administered with or without food.
- If as dose is missed, take the missed dose as soon as possible. Do not double the next dose.
- Assess LDL-C when clinically appropriate, as early as 4 weeks after initiating ZETIA.
- Administer ZETIA at least 2 hours before or 4 hours after administration of a bile acid sequestrant [see Drug Interactions (7)].

3 DOSAGE FORMS AND STRENGTHS

Tablets: 10-mg white to off-white, capsule-shaped, and debossed with "414" on one side.

4 CONTRAINDICATIONS

ZETIA is contraindicated in patients with a known hypersensitivity to ezetimibe or any of the excipients in ZETIA. Hypersensitivity reactions including anaphylaxis, angioedema, rash, and urticaria have been reported [see Adverse Reactions (6.2)].

When used in combination with a statin, fenofibrate, or other LDL-C lowering therapy, ZETIA is contraindicated in patients for whom a statin, fenofibrate, or other LDL-C lowering therapy are contraindicated. Refer to the Prescribing Information of these products for a list of their contraindications [see Warnings and Precautions (5.1)].

5 WARNINGS AND PRECAUTIONS

5.1 Risks Associated with Combination Treatment with a Statin, Fenofibrate, or Other LDL-C Lowering Therapies

If ZETIA is administered with a statin, fenofibrate, or other LDL-C lowering therapies, refer to the Prescribing Information of these products for a description of their risks including, but not limited to, the warnings and precautions [see Contraindications (4)].

5.2 Liver Enzymes

Increases in serum transaminases have been reported with use of ZETIA [see Adverse Reactions (6.1)]. In controlled clinical combination studies of ZETIA initiated concurrently with a statin, the incidence of consecutive elevations (≥3 × ULN) in hepatic transaminase levels was 1.3% for patients treated with ZETIA administered with statins and 0.4% for patients treated with statins alone. Perform liver enzyme testing as clinically indicated and consider withdrawal of ZETIA if increases in ALT or AST ≥3 × ULN persist.

5.3 Myopathy/Rhabdomyolysis

ZETIA may cause myopathy [muscle pain, tenderness, or weakness associated with elevated creatine kinase (CK)] and rhabdomyolysis [see Adverse Reactions (6.1)]. In post-marketing reports, most patients who developed rhabdomyolysis were taking a statin or other agents known to be associated with an increased risk of rhabdomyolysis, such as fibrates. If myopathy is suspected, discontinue ZETIA and other concomitant medications, as appropriate.

6 ADVERSE REACTIONS

The following serious adverse reactions are discussed in greater detail in other sections of the label:

- Liver enzyme abnormalities [see Warnings and Precautions (5.2)]
- Rhabdomyolysis and myopathy [see Warnings and Precautions (5.3)]

6.1 Clinical Trials Experience

Because clinical studies are conducted under widely varying conditions, adverse reaction rates observed in the clinical studies of a drug cannot be directly compared to rates in the clinical studies of another drug and may not reflect the rates observed in clinical practice.

Monotherapy

In 10 double-blind, placebo-controlled clinical trials, 2,396 patients with primary hyperlipidemia (age range 9 to 86 years; 50% female, 90% White, 5% Black or African American, 2% Asian, 3% other races; 3% identified as Hispanic or Latino ethnicity) and elevated LDL-C were treated with ZETIA 10 mg daily for a median treatment duration of 12 weeks (range 0 to 39 weeks).

Adverse reactions reported in ≥2% of patients treated with ZETIA and at an incidence greater than placebo in placebo-controlled studies of ZETIA are shown in Table 1.

TABLE 1: Adverse Reactions Occurring ≥2% and Greater than Placebo in ZETIA-treated Patients
Adverse Reaction | Placebo (%) n = 1,159 | ZETIA 10 mg (%) n = 2,396
Upper respiratory tract infection | 2.5 | 4.3
Diarrhea | 3.7 | 4.1
Arthralgia | 2.2 | 3.0
Sinusitis | 2.2 | 2.8
Pain in extremity | 2.5 | 2.7
Fatigue | 1.5 | 2.4
Influenza | 1.5 | 2.0

Combination with a Statin

In 28 double-blind, controlled (placebo or active-controlled) clinical trials, 11,308 patients with primary hyperlipidemia (age range 10 to 93 years, 48% female, 85% White, 7% Black or African American, 3% Asian, 5% other races; 4% identified as Hispanic or Latino ethnicity) and elevated LDL-C were treated with ZETIA 10 mg/day concurrently with or added to on-going statin therapy for a median treatment duration of 8 weeks (range 0 to 112 weeks).

The incidence of consecutive increased transaminases (≥3 × ULN) was higher in patients receiving ZETIA administered with statins (1.3%) than in patients treated with statins alone (0.4%).

Adverse reactions reported in ≥2% of patients treated with ZETIA + statin and at an incidence greater than statin are shown in Table 2.

TABLE 2: Adverse Reactions Occurring ≥2% in ZETIA-treated Patients Coadministered with a Statin and at an Incidence Greater than Statin
Adverse Reaction | All Statins [All Statins = all doses of all statins] (%) n = 9,361 | ZETIA + All Statins (%) n = 11,308
Nasopharyngitis | 3.3 | 3.7
Myalgia | 2.7 | 3.2
Upper respiratory tract infection | 2.8 | 2.9
Arthralgia | 2.4 | 2.6
Diarrhea | 2.2 | 2.5
Back pain | 2.3 | 2.4
Influenza | 2.1 | 2.2
Pain in extremity | 1.9 | 2.1
Fatigue | 1.6 | 2.0

Combination with Fenofibrate

This clinical trial involving 625 patients with mixed dyslipidemia (age range 20 to 76 years; 44% female, 79% White, 1% Black or African American, 20% other races; 11% identified as Hispanic or Latino ethnicity) treated for up to 12 weeks and 576 patients treated for up to an additional 48 weeks evaluated coadministration of ZETIA and fenofibrate. Incidence rates for clinically important elevations (≥3 × ULN, consecutive) in hepatic transaminase levels were 4.5% and 2.7% for fenofibrate monotherapy (n=188) and ZETIA coadministered with fenofibrate (n=183), respectively, adjusted for treatment exposure. Corresponding incidence rates for cholecystectomy were 0.6% and 1.7% for fenofibrate monotherapy and ZETIA coadministered with fenofibrate, respectively [see Drug Interactions (7)].

6.2 Post-Marketing Experience

Because the reactions below are reported voluntarily from a population of uncertain size, it is generally not possible to reliably estimate their frequency or establish a causal relationship to drug exposure.

The following additional adverse reactions have been identified during post-approval use of ZETIA:

Blood Disorders: thrombocytopenia

Gastrointestinal Disorders: abdominal pain; pancreatitis; nausea

Hepatobiliary Disorders: elevations in liver transaminases, including elevations more than 5 X ULN; hepatitis; cholelithiasis; cholecystitis

Immune System Disorders: Hypersensitivity reactions including: anaphylaxis, angioedema, rash, and urticaria

Musculoskeletal Disorders: elevated creatine phosphokinase; myopathy/rhabdomyolysis

Nervous System Disorders: dizziness; paresthesia; depression; headache

Skin and Subcutaneous Tissue Disorders: erythema multiforme

7 DRUG INTERACTIONS

Table 3 includes a list of drugs with clinically important drug interactions when administered concomitantly with ZETIA and instructions for preventing or managing them.

Table 3: Clinically Important Drug Interactions with ZETIA
Cyclosporine
Clinical Impact: | Concomitant use of ZETIA and cyclosporine increases ezetimibe and cyclosporine concentrations. The degree of increase in ezetimibe exposure may be greater in patients with severe renal insufficiency [see Clinical Pharmacology (12.3)].
Intervention: | Monitor cyclosporine concentrations in patients receiving ZETIA and cyclosporine. In patients treated with cyclosporine, weigh the potential effects of the increased exposure to ezetimibe from concomitant use against the benefits of alterations in lipid levels provided by ZETIA.
Fibrates
Clinical Impact: | Both fenofibrate and ezetimibe may increase cholesterol excretion into the bile, leading to cholelithiasis. Co-administration of ZETIA with fibrates other than fenofibrate is not recommended [see Adverse Reactions (6.1)].
Intervention: | If cholelithiasis is suspected in a patient receiving ZETIA and fenofibrate, gallbladder studies are indicated, and alternative lipid-lowering therapy should be considered.
Bile Acid Sequestrants
Clinical Impact: | Concomitant cholestyramine administration decreased the mean exposure of total ezetimibe. This may result in a reduction of efficacy [see Clinical Pharmacology (12.3)].
Intervention: | In patients taking a bile acid sequestrant, administer ZETIA at least 2 hours before or 4 hours after the bile acid sequestrant [see Dosage and Administration (2)].

8 USE IN SPECIFIC POPULATIONS

8.1 Pregnancy

Risk Summary

There are insufficient data on ezetimibe use in pregnant women to evaluate for a drug-associated risk of major birth defects, miscarriage or adverse maternal or fetal outcomes. In animal reproduction studies, no adverse developmental effects were observed in pregnant rats and rabbits orally administered ezetimibe during the period of organogenesis at doses that resulted in up to 10 and 150 times, respectively, the human exposure at the MRHD, based on AUC (see Data). ZETIA should be used during pregnancy only if the potential benefit justifies the potential risk to the fetus. When ZETIA is administered with a statin, refer to the Prescribing Information for the statin.

The estimated background risk of major birth defects and miscarriage for the indicated population is unknown. In the U.S. general population, the estimated risk of major birth defects and miscarriage in clinically recognized pregnancies is 2 to 4% and 15 to 20%, respectively.

Data

Animal Data

In oral (gavage) embryo-fetal development studies of ezetimibe conducted in rats (gestation days 6-15) and rabbits (gestation days 7-19), there was no evidence of maternal toxicity or embryolethal effects at the doses tested (250, 500, 1,000 mg/kg/day). In rats, increased incidences of common fetal skeletal findings (extra pair of thoracic ribs, unossified cervical vertebral centra, shortened ribs) were observed at 1,000 mg/kg/day (~10 times the human exposure at 10 mg daily based on AUC0-24hr for total ezetimibe). In rabbits treated with ezetimibe, an increased incidence of extra thoracic ribs was observed at 1,000 mg/kg/day (150 times the human exposure at 10 mg daily based on AUC0-24hr for total ezetimibe). The animal-to-human exposure multiple for total ezetimibe at the no-observed effect level was 6 times for rat and 134 times for rabbit. Fetal exposure to ezetimibe (conjugated and unconjugated) was confirmed in subsequent placental transfer studies conducted using a maternal dose of 1,000 mg/kg/day. The fetal maternal plasma exposure ratio (total ezetimibe) was 1.5 for rats on gestation day 20 and 0.03 for rabbits on gestation day 22.

The effect of ezetimibe on prenatal and postnatal development and maternal function was evaluated in pregnant rats at doses of 100, 300 or 1,000 mg/kg/day from gestation day 6 through lactation day 21. No maternal toxicity or adverse developmental outcomes were observed up to and including the highest dose tested (17 times the human exposure at 10 mg daily based on AUC0-24hr for total ezetimibe).

Multiple-dose studies of ezetimibe given in combination with statins in rats and rabbits during organogenesis resulted in higher ezetimibe and statin exposures. Reproductive findings occurred at lower doses in combination therapy compared to monotherapy.

8.2 Lactation

Risk Summary
There is no information about the presence of ezetimibe in human milk. Ezetimibe is present in rat milk (see Data). When a drug is present in animal milk, it is likely that the drug will be present in human milk. There is no information about the effects of ezetimibe on the breastfed infant or the effects of ezetimibe on milk production. ZETIA should not be used in nursing mothers unless the potential benefit justifies the potential risk to the infant.

Data
Ezetimibe was present in the milk of lactating rats. The pup to maternal plasma ratio for total ezetimibe was 0.5 on lactation day 12.

8.4 Pediatric Use

The safety and effectiveness of ZETIA in combination with a statin as an adjunct to diet to reduce LDL-C have been established in pediatric patients 10 years of age and older with HeFH. Use of ZETIA for this indication is based on a double-blind, placebo-controlled clinical trial in 248 pediatric patients (142 males and 106 postmenarchal females) 10 years of age and older with HeFH [see Clinical Studies (14)]. In this limited controlled trial, there was no significant effect on growth or sexual maturation in the adolescent males or females, or on menstrual cycle length in females.

The safety and effectiveness of ZETIA in combination with a statin, and other LDL-C lowering therapies, to reduce LDL-C have been established in pediatric patients 10 years of age and older with HoFH. Use of ZETIA for this indication is based on a 12-week double-blind, placebo-controlled clinical trial followed by an uncontrolled extension period in 7 pediatric patients 11 years of age and older with HoFH [see Clinical Studies (14)].

The safety and effectiveness of ZETIA as an adjunct to diet for the reduction of elevated sitosterol and campesterol levels have been established in adults and pediatric patients 9 years of age and older with homozygous familial sitosterolemia. Use of ZETIA for this indication is based on an 8-week double-blind, placebo-controlled clinical trial in 4 patients 9 years of age and older with homozygous sitosterolemia with elevated plasma sitosterol levels (>5 mg/dL) [see Clinical Studies (14)].

The safety and effectiveness of ZETIA have not been established in pediatric patients younger than 10 years of age with HeFH or HoFH, in pediatric patients younger than 9 years of age with homozygous familial sitosterolemia, or in pediatric patients with other types of hyperlipidemia.

8.5 Geriatric Use

Of the 2,396 patients who received ZETIA in clinical trials, 669 (28%) were 65 years of age and older, and 111 (5%) were 75 years of age and older. Of the 11,308 patients who received ZETIA in combination with a statin in clinical trials, 3587 (32%) were 65 years of age and older, and 924 (8%) were 75 years of age and older [see Clinical Studies (14)]. No overall differences in safety or effectiveness of ZETIA have been observed between patients 65 years of age and older and younger patients. No clinically meaningful differences in the pharmacokinetics of ezetimibe were observed in geriatric patients compared to younger adult patients [see Clinical Pharmacology (12.3)].

8.6 Renal Impairment

No dosage adjustment of ZETIA is necessary in patients with renal impairment.

8.7 Hepatic Impairment

ZETIA is not recommended for use in patients with moderate to severe hepatic impairment (Child-Pugh B or C) due to the unknown effects of the increased exposure to ezetimibe [see Clinical Pharmacology (12.3)].

10 OVERDOSAGE

In the event of overdose, consider contacting the Poison Help line (1-800-222-1222) or a medical toxicologist for additional overdosage management recommendations.

11 DESCRIPTION

ZETIA (ezetimibe) is a dietary cholesterol absorption inhibitor. The chemical name of ezetimibe is 1-(4-fluorophenyl)-3(R)-[3-(4-fluorophenyl)-3(S)-hydroxypropyl]-4(S)-(4-hydroxyphenyl)-2-azetidinone. The empirical formula is C24H21F2NO3. Its molecular weight is 409.4 and its structural formula is:

Ezetimibe is a white, crystalline powder that is freely to very soluble in ethanol, methanol, and acetone and practically insoluble in water. Ezetimibe has a melting point of about 163°C and is stable at ambient temperature. ZETIA is available as a tablet for oral use containing 10 mg of ezetimibe and the following inactive ingredients: croscarmellose sodium NF, lactose monohydrate NF, magnesium stearate NF, microcrystalline cellulose NF, povidone USP, and sodium lauryl sulfate NF.

12 CLINICAL PHARMACOLOGY

12.1 Mechanism of Action

Ezetimibe reduces blood cholesterol by inhibiting the absorption of cholesterol by the small intestine.

The molecular target of ezetimibe has been shown to be the sterol transporter, Niemann-Pick C1-Like 1 (NPC1L1), which is involved in the intestinal uptake of cholesterol and phytosterols. Ezetimibe localizes at the brush border of the small intestine and inhibits the absorption of cholesterol, leading to a decrease in the delivery of intestinal cholesterol to the liver. This causes a reduction of hepatic cholesterol stores and an increase in LDL receptors, resulting in clearance of cholesterol from the blood.

12.2 Pharmacodynamics

ZETIA reduces total cholesterol (total-C), LDL-C, apolipoprotein (Apo) B, and non-high-density lipoprotein cholesterol (non-HDL-C) in patients with hyperlipidemia.

In a 2-week clinical trial in 18 hypercholesterolemic patients, ZETIA inhibited intestinal cholesterol absorption by 54%, compared with placebo. ZETIA had no clinically meaningful effect on the plasma concentrations of the fat-soluble vitamins A, D, and E (in a trial of 113 patients) and did not impair adrenocortical steroid hormone production (in a trial of 118 patients).

12.3 Pharmacokinetics

Absorption

After oral administration, ezetimibe is absorbed and extensively conjugated to a pharmacologically active phenolic glucuronide (ezetimibe-glucuronide). After a single 10-mg dose of ZETIA to fasted adults, mean ezetimibe peak plasma concentrations (Cmax) of 3.4 to 5.5 ng/mL were attained within 4 to 12 hours (Tmax). Ezetimibe-glucuronide mean Cmax values of 45 to 71 ng/mL were achieved between 1 and 2 hours (Tmax). There was no substantial deviation from dose proportionality between 5 and 20 mg. The absolute bioavailability of ezetimibe cannot be determined, as the compound is virtually insoluble in aqueous media suitable for injection.

Effect of Food

Concomitant food administration (high-fat or non-fat meals) had no effect on the extent of absorption of ezetimibe when administered as ZETIA 10-mg tablets. The Cmax value of ezetimibe was increased by 38% with consumption of high-fat meals.

Distribution

Ezetimibe and ezetimibe-glucuronide are highly bound (>90%) to human plasma proteins.

Elimination
Metabolism

Ezetimibe is primarily metabolized in the small intestine and liver via glucuronide conjugation (a phase II reaction) with subsequent biliary and renal excretion. Minimal oxidative metabolism (a phase I reaction) has been observed in all species evaluated. In humans, ezetimibe is rapidly metabolized to ezetimibe-glucuronide. Ezetimibe and ezetimibe-glucuronide are the major drug-derived compounds detected in plasma, constituting approximately 10 to 20% and 80 to 90% of the total drug in plasma, respectively.

Both ezetimibe and ezetimibe-glucuronide are eliminated from plasma with a half-life of approximately 22 hours for both ezetimibe and ezetimibe-glucuronide. Plasma concentration-time profiles exhibit multiple peaks, suggesting enterohepatic recycling.

Excretion

Following oral administration of ^14C-ezetimibe (20 mg) to human subjects, total ezetimibe (ezetimibe + ezetimibe-glucuronide) accounted for approximately 93% of the total radioactivity in plasma. After 48 hours, there were no detectable levels of radioactivity in the plasma.

Approximately 78% and 11% of the administered radioactivity were recovered in the feces and urine, respectively, over a 10-day collection period. Ezetimibe was the major component in feces and accounted for 69% of the administered dose, while ezetimibe-glucuronide was the major component in urine and accounted for 9% of the administered dose.

Specific Populations
Geriatric Patients

In a multiple-dose trial with ezetimibe given 10 mg once daily for 10 days, plasma concentrations for total ezetimibe were about 2-fold higher in older (≥65 years) healthy subjects compared to younger subjects. However, the difference in plasma concentrations is not clinically meaningful.

Gender

In a multiple-dose trial with ezetimibe given 10 mg once daily for 10 days, plasma concentrations for total ezetimibe were slightly higher (<20%) in females than in males.

Race

Based on a meta-analysis of multiple-dose pharmacokinetic studies, there were no pharmacokinetic differences between Black and White subjects. Studies in Asian subjects indicated that the pharmacokinetics of ezetimibe were similar to those seen in White subjects.

Renal Impairment

After a single 10-mg dose of ezetimibe in patients with severe renal disease (n=8; mean CrCl ≤30 mL/min/1.73 m^2), the mean AUC values for total ezetimibe, ezetimibe-glucuronide, and ezetimibe were increased approximately 1.5-fold, compared to healthy subjects (n=9).

Hepatic Impairment

After a single 10-mg dose of ezetimibe, the mean AUC for total ezetimibe was increased approximately 1.7-fold in patients with mild hepatic impairment (Child-Pugh score 5 to 6), compared to healthy subjects. The mean AUC values for total ezetimibe and ezetimibe were increased approximately 3- to 4-fold and 5- to 6-fold, respectively, in patients with moderate (Child-Pugh score 7 to 9) or severe hepatic impairment (Child-Pugh score 10 to 15). In a 14-day, multiple-dose trial (10 mg daily) in patients with moderate hepatic impairment, the mean AUC values for total ezetimibe and ezetimibe were increased approximately 4-fold on Day 1 and Day 14 compared to healthy subjects [see Use in Specific Populations (8.7)].

Drug Interactions

ZETIA had no significant effect on a series of probe drugs (caffeine, dextromethorphan, tolbutamide, and IV midazolam) known to be metabolized by cytochrome P450 (1A2, 2D6, 2C8/9 and 3A4) in a “cocktail” trial of twelve healthy adult males. This indicates that ezetimibe is neither an inhibitor nor an inducer of these cytochrome P450 isozymes, and it is unlikely that ezetimibe will affect the metabolism of drugs that are metabolized by these enzymes.

TABLE 4: Effect of Coadministered Drugs on Total Ezetimibe
Coadministered Drug and Dosing Regimen | Total Ezetimibe [Based on 10-mg dose of ezetimibe.]
 | Change in AUC | Change in Cmax
Cyclosporine-stable dose required (75-150 mg BID) [Post-renal transplant patients with mild impaired or normal renal function. In a different trial, a renal transplant patient with severe renal insufficiency (creatinine clearance of 13.2 mL/min/1.73 m^2) who was receiving multiple medications, including cyclosporine, demonstrated a 12-fold greater exposure to total ezetimibe compared to healthy subjects.] , [See Drug Interactions (7).] | ↑240% | ↑290%
Fenofibrate, 200 mg QD, 14 days | ↑48% | ↑64%
Gemfibrozil, 600 mg BID, 7 days | ↑64% | ↑91%
Cholestyramine, 4 g BID, 14 days | ↓55% | ↓4%
Aluminum & magnesium hydroxide combination antacid, single dose [Supralox, 20 mL.] | ↓4% | ↓30%
Cimetidine, 400 mg BID, 7 days | ↑6% | ↑22%
Glipizide, 10 mg, single dose | ↑4% | ↓8%
Statins
Lovastatin 20 mg QD, 7 days | ↑9% | ↑3%
Pravastatin 20 mg QD, 14 days | ↑7% | ↑23%
Atorvastatin 10 mg QD, 14 days | ↓2% | ↑12%
Rosuvastatin 10 mg QD, 14 days | ↑13% | ↑18%
Fluvastatin 20 mg QD, 14 days | ↓19% | ↑7%

TABLE 5: Effect of Ezetimibe Coadministration on Systemic Exposure to Other Drugs
Coadministered Drug and its Dosage Regimen | Ezetimibe Dosage Regimen | Change in AUC of Coadministered Drug | Change in Cmax of Coadministered Drug
Warfarin, 25-mg single dose on Day 7 | 10 mg QD, 11 days | ↓2% (R-warfarin) ↓4% (S-warfarin) | ↑3% (R-warfarin) ↑1% (S-warfarin)
Digoxin, 0.5-mg single dose | 10 mg QD, 8 days | ↑2% | ↓7%
Gemfibrozil, 600 mg BID, 7 days [See Drug Interactions (7).] | 10 mg QD, 7 days | ↓1% | ↓11%
Ethinyl estradiol & Levonorgestrel, QD, 21 days | 10 mg QD, days 8-14 of 21d oral contraceptive cycle | Ethinyl estradiol 0% Levonorgestrel 0% | Ethinyl estradiol ↓9% Levonorgestrel ↓5%
Glipizide, 10 mg on Days 1 and 9 | 10 mg QD, days 2-9 | ↓3% | ↓5%
Fenofibrate, 200 mg QD, 14 days | 10 mg QD, 14 days | ↑11% | ↑7%
Cyclosporine, 100-mg single dose Day 7 | 20 mg QD, 8 days | ↑15% | ↑10%
Statins
Lovastatin 20 mg QD, 7 days | 10 mg QD, 7 days | ↑19% | ↑3%
Pravastatin 20 mg QD, 14 days | 10 mg QD, 14 days | ↓20% | ↓24%
Atorvastatin 10 mg QD, 14 days | 10 mg QD, 14 days | ↓4% | ↑7%
Rosuvastatin 10 mg QD, 14 days | 10 mg QD, 14 days | ↑19% | ↑17%
Fluvastatin 20 mg QD, 14 days | 10 mg QD, 14 days | ↓39% | ↓27%

13 NONCLINICAL TOXICOLOGY

13.1 Carcinogenesis, Mutagenesis, Impairment of Fertility

A 104-week dietary carcinogenicity study with ezetimibe was conducted in rats at doses up to 1,500 mg/kg/day (males) and 500 mg/kg/day (females) (~20 × the human exposure at 10 mg daily based on AUC0-24hr for total ezetimibe). A 104-week dietary carcinogenicity study with ezetimibe was also conducted in mice at doses up to 500 mg/kg/day (>150 × the human exposure at 10 mg daily based on AUC0-24hr for total ezetimibe). There were no statistically significant increases in tumor incidences in drug-treated rats or mice.

No evidence of mutagenicity was observed in vitro in a microbial mutagenicity (Ames) test with Salmonella typhimurium and Escherichia coli with or without metabolic activation. No evidence of clastogenicity was observed in vitro in a chromosomal aberration assay in human peripheral blood lymphocytes with or without metabolic activation. In addition, there was no evidence of genotoxicity in the in vivo mouse micronucleus test.

In oral (gavage) fertility studies of ezetimibe conducted in rats, there was no evidence of reproductive toxicity at doses up to 1,000 mg/kg/day in male or female rats (~7 × the human exposure at 10 mg daily based on AUC0-24hr for total ezetimibe).

14 CLINICAL STUDIES

Primary Hyperlipidemia in Adults

ZETIA reduces total-C, LDL-C, Apo B, and non-HDL-C in patients with hyperlipidemia. Maximal to near maximal response is generally achieved within 2 weeks and maintained during chronic therapy.

Monotherapy

In two multicenter, double-blind, placebo-controlled, 12-week trials in 1719 patients (age range 18 to 86 years, 52% females; 91% White, 5% Black or African American, 1% Asian, 3% other races mostly identified as Hispanic or Latino ethnicity) with primary hyperlipidemia, ZETIA significantly lowered total-C, LDL-C, Apo B, and non-HDL-C compared to placebo (see Table 6). Reduction in LDL-C was consistent across age, sex, and baseline LDL-C.

TABLE 6: Response to ZETIA in Patients with Primary Hyperlipidemia (Mean % Change from Untreated Baseline [Baseline - on no lipid-lowering drug.])
 | Treatment Group | N | Total-C | LDL-C | Apo B | Non-HDL-C
Trial 1 [ZETIA significantly reduced total-C, LDL-C, Apo B, and non-HDL-C compared to placebo.] | Placebo | 205 | +1 | +1 | -1 | +1
Trial 1 [ZETIA significantly reduced total-C, LDL-C, Apo B, and non-HDL-C compared to placebo.] | Ezetimibe | 622 | -12 | -18 | -15 | -16
Trial 2 | Placebo | 226 | +1 | +1 | -1 | +2
Trial 2 | Ezetimibe | 666 | -12 | -18 | -16 | -16
Pooled Data (Trials 1 & 2) | Placebo | 431 | 0 | +1 | -2 | +1
Pooled Data (Trials 1 & 2) | Ezetimibe | 1288 | -13 | -18 | -16 | -16

Combination with Statins: ZETIA Added to On-going Statin Therapy

In a multicenter, double-blind, placebo-controlled, 8-week trial, 769 patients (age range 22 to 85 years, 42% females; 90% White, 6% Black or African American, 1% Asian, 3% other races; and 2% identified as Hispanic or Latino ethnicity) with primary hyperlipidemia, known coronary heart disease or multiple cardiovascular risk factors who were already receiving statin monotherapy but who had not met their NCEP ATP II target LDL-C goal, were randomized to receive either ZETIA or placebo in addition to their on-going statin.

ZETIA, added to on-going statin therapy, significantly lowered total-C, LDL-C, Apo B, and non-HDL-C compared with a statin administered alone (see Table 7). LDL-C reductions induced by ZETIA were generally consistent across all statins.

TABLE 7: Response to Addition of ZETIA to On-Going Statin Therapy [Patients receiving each statin: 40% atorvastatin, 31% simvastatin, 29% others (pravastatin, fluvastatin, cerivastatin, lovastatin).] in Patients with Hyperlipidemia (Mean % Change from Treated Baseline [Baseline - on a statin alone.])
Treatment (Daily Dose) | N | Total-C | LDL-C | Apo B | Non-HDL-C
On-going Statin + Placebo [ZETIA + statin significantly reduced total-C, LDL-C, Apo B, and non-HDL-C compared to statin alone.] | 390 | -2 | -4 | -3 | -3
On-going Statin + ZETIA | 379 | -17 | -25 | -19 | -23

Combination with Statins: ZETIA Initiated Concurrently with a Statin

In four multicenter, double-blind, placebo-controlled, 12-week trials, in 2,382 patients (age range 18 to 87 years, 57% female; 88% White, 5% Black or African American, 2% Asian, 5% other races mostly identified as Hispanic or Latino) with hyperlipidemia, ZETIA or placebo was administered alone or with various doses of atorvastatin, simvastatin, pravastatin, or lovastatin.

When all patients receiving ZETIA with a statin were compared to all those receiving the corresponding statin alone, ZETIA significantly lowered total-C, LDL-C, Apo B, and non-HDL-C compared to the statin administered alone. LDL-C reductions induced by ZETIA were generally consistent across all statins. (See footnote , Tables 8 to 11.)

TABLE 8: Response to ZETIA and Atorvastatin Initiated Concurrently in Patients with Primary Hyperlipidemia (Mean % Change from Untreated Baseline [Baseline - on no lipid-lowering drug.])
Treatment (Daily Dose) | N | Total-C | LDL-C | Apo B | Non-HDL-C
Placebo | 60 | +4 | +4 | +3 | +4
ZETIA | 65 | -14 | -20 | -15 | -18
Atorvastatin 10 mg | 60 | -26 | -37 | -28 | -34
ZETIA + Atorvastatin 10 mg | 65 | -38 | -53 | -43 | -49
Atorvastatin 20 mg | 60 | -30 | -42 | -34 | -39
ZETIA + Atorvastatin 20 mg | 62 | -39 | -54 | -44 | -50
Atorvastatin 40 mg | 66 | -32 | -45 | -37 | -41
ZETIA + Atorvastatin 40 mg | 65 | -42 | -56 | -45 | -52
Atorvastatin 80 mg | 62 | -40 | -54 | -46 | -51
ZETIA + Atorvastatin 80 mg | 63 | -46 | -61 | -50 | -58
Pooled data (All Atorvastatin Doses) [ZETIA + all doses of atorvastatin pooled (10-80 mg) significantly reduced total-C, LDL-C, Apo B, and non-HDL-C compared to all doses of atorvastatin pooled (10-80 mg).] | 248 | -32 | -44 | -36 | -41
Pooled data (All ZETIA + Atorvastatin Doses) | 255 | -41 | -56 | -45 | -52

TABLE 9: Response to ZETIA and Simvastatin Initiated Concurrently in Patients with Primary Hyperlipidemia (Mean % Change from Untreated Baseline [Baseline - on no lipid-lowering drug.])
Treatment (Daily Dose) | N | Total-C | LDL-C | Apo B | Non-HDL-C
Placebo | 70 | -1 | -1 | 0 | -1
ZETIA | 61 | -13 | -19 | -14 | -17
Simvastatin 10 mg | 70 | -18 | -27 | -21 | -25
ZETIA + Simvastatin 10 mg | 67 | -32 | -46 | -35 | -42
Simvastatin 20 mg | 61 | -26 | -36 | -29 | -33
ZETIA + Simvastatin 20 mg | 69 | -33 | -46 | -36 | -42
Simvastatin 40 mg | 65 | -27 | -38 | -32 | -35
ZETIA + Simvastatin 40 mg | 73 | -40 | -56 | -45 | -51
Simvastatin 80 mg | 67 | -32 | -45 | -37 | -41
ZETIA + Simvastatin 80 mg | 65 | -41 | -58 | -47 | -53
Pooled data (All Simvastatin Doses) [ZETIA + all doses of simvastatin pooled (10-80 mg) significantly reduced total-C, LDL-C, Apo B, and non-HDL-C compared to all doses of simvastatin pooled (10-80 mg).] | 263 | -26 | -36 | -30 | -34
Pooled data (All ZETIA + Simvastatin Doses) | 274 | -37 | -51 | -41 | -47

TABLE 10: Response to ZETIA and Pravastatin Initiated Concurrently in Patients with Primary Hyperlipidemia (Mean % Change from Untreated Baseline [Baseline - on no lipid-lowering drug.])
Treatment (Daily Dose) | N | Total-C | LDL-C | Apo B | Non-HDL-C
Placebo | 65 | 0 | -1 | -2 | 0
ZETIA | 64 | -13 | -20 | -15 | -17
Pravastatin 10 mg | 66 | -15 | -21 | -16 | -20
ZETIA + Pravastatin 10 mg | 71 | -24 | -34 | -27 | -32
Pravastatin 20 mg | 69 | -15 | -23 | -18 | -20
ZETIA + Pravastatin 20 mg | 66 | -27 | -40 | -31 | -36
Pravastatin 40 mg | 70 | -22 | -31 | -26 | -28
ZETIA + Pravastatin 40 mg | 67 | -30 | -42 | -32 | -39
Pooled data (All Pravastatin Doses) [ZETIA + all doses of pravastatin pooled (10-40 mg) significantly reduced total-C, LDL-C, Apo B, and non-HDL-C compared to all doses of pravastatin pooled (10-40 mg).] | 205 | -17 | -25 | -20 | -23
Pooled data (All ZETIA + Pravastatin Doses) | 204 | -27 | -39 | -30 | -36

TABLE 11: Response to ZETIA and Lovastatin Initiated Concurrently in Patients with Primary Hyperlipidemia (Mean % Change from Untreated Baseline [Baseline - on no lipid-lowering drug.])
Treatment (Daily Dose) | N | Total-C | LDL-C | Apo B | Non-HDL-C
Placebo | 64 | +1 | 0 | +1 | +1
ZETIA | 72 | -13 | -19 | -14 | -16
Lovastatin 10 mg | 73 | -15 | -20 | -17 | -19
ZETIA + Lovastatin 10 mg | 65 | -24 | -34 | -27 | -31
Lovastatin 20 mg | 74 | -19 | -26 | -21 | -24
ZETIA + Lovastatin 20 mg | 62 | -29 | -41 | -34 | -39
Lovastatin 40 mg | 73 | -21 | -30 | -25 | -27
ZETIA + Lovastatin 40 mg | 65 | -33 | -46 | -38 | -43
Pooled data (All Lovastatin Doses) [ZETIA + all doses of lovastatin pooled (10-40 mg) significantly reduced total-C, LDL-C, Apo B, and non-HDL-C compared to all doses of lovastatin pooled (10-40 mg).] | 220 | -18 | -25 | -21 | -23
Pooled data (All ZETIA + Lovastatin Doses) | 192 | -29 | -40 | -33 | -38

Combination with Fenofibrate

In a multicenter, double-blind, placebo-controlled, clinical trial in patients with mixed hyperlipidemia, 625 patients (age range 20 to 76 years, 44% female; 79% White, 1% Black or African American, 20% other races; and 11% identified as Hispanic or Latino ethnicity) were treated for up to 12 weeks and 576 for up to an additional 48 weeks. Patients were randomized to receive placebo, ZETIA alone, 160 mg fenofibrate alone, or ZETIA and 160 mg fenofibrate in the 12-week trial. After completing the 12-week trial, eligible patients were assigned to ZETIA coadministered with fenofibrate or fenofibrate monotherapy for an additional 48 weeks.

ZETIA coadministered with fenofibrate significantly lowered total-C, LDL-C, Apo B, and non-HDL-C compared to fenofibrate administered alone (see Table 12).

TABLE 12: Response to ZETIA and Fenofibrate Initiated Concurrently in Patients with Mixed Hyperlipidemia (Mean % Change from Untreated Baseline [Baseline - on no lipid-lowering drug.] at 12 weeks)
Treatment (Daily Dose) | N | Total-C | LDL-C | Apo B | Non-HDL-C
Placebo | 63 | 0 | 0 | -1 | 0
ZETIA | 185 | -12 | -13 | -11 | -15
Fenofibrate 160 mg | 188 | -11 | -6 | -15 | -16
ZETIA + Fenofibrate 160 mg | 183 | -22 | -20 | -26 | -30

The changes in lipid endpoints after an additional 48 weeks of treatment with ZETIA coadministered with fenofibrate or with fenofibrate alone were consistent with the 12-week data displayed above.

HeFH in Pediatric Patients

The effects of ZETIA coadministered with simvastatin (n=126) compared to simvastatin monotherapy (n=122) have been evaluated in males and females with HeFH. In a multicenter, double-blind, controlled trial followed by an open-label phase, 142 males and 106 postmenarchal females, 10 to 17 years of age (mean age 14.2 years, 43% females, 82% White, 4% Asian, 2% Black or African American, 13% multi-racial; 14% identified as Hispanic or Latino ethnicity) with HeFH were randomized to receive either ZETIA coadministered with simvastatin or simvastatin monotherapy. Inclusion in the trial required 1) a baseline LDL-C level between 160 and 400 mg/dL and 2) a medical history and clinical presentation consistent with HeFH. The mean baseline LDL-C value was 225 mg/dL (range: 161 to 351 mg/dL) in the ZETIA coadministered with simvastatin group compared to 219 mg/dL (range: 149 to 336 mg/dL) in the simvastatin monotherapy group. The patients received coadministered ZETIA and simvastatin (10 mg, 20 mg, or 40 mg) or simvastatin monotherapy (10 mg, 20 mg, or 40 mg) for 6 weeks, coadministered ZETIA and 40-mg simvastatin or 40-mg simvastatin monotherapy for the next 27 weeks, and open-label coadministered ZETIA and simvastatin (10 mg, 20 mg, or 40 mg) for 20 weeks thereafter.

The results of the trial at Week 6 are summarized in Table 13. Results at Week 33 were consistent with those at Week 6.

TABLE 13: Mean Percent Difference at Week 6 Between the Pooled ZETIA Coadministered with Simvastatin Group and the Pooled Simvastatin Monotherapy Group in Adolescent Patients with HeFH
 | Total-C | LDL-C | Apo B | Non-HDL-C
Mean percent difference between treatment groups | -12% | -15% | -12% | -14%
95% Confidence Interval | (-15%, -9%) | (-18%, -12%) | (-15%, -9%) | (-17%, -11%)

HoFH in Adults and Pediatric Patients

A trial was conducted to assess the efficacy of ZETIA in the treatment of HoFH. This double-blind, randomized, 12-week trial enrolled 50 patients (age range 11 to 74 years, 58% female; 90% White, 2% Black or African American, 8% other races identified as Hispanic or Latino) with a clinical and/or genotypic diagnosis of HoFH, with or without concomitant LDL apheresis, already receiving atorvastatin or simvastatin (40 mg). Patients were randomized to one of three treatment groups, atorvastatin or simvastatin (80 mg), ZETIA administered with atorvastatin or simvastatin (40 mg), or ZETIA administered with atorvastatin or simvastatin (80 mg). Due to decreased bioavailability of ezetimibe in patients concomitantly receiving cholestyramine [see Drug Interactions (7)], ezetimibe was dosed at least 4 hours before or after administration of resins. Mean baseline LDL-C was 341 mg/dL in those patients randomized to atorvastatin 80 mg or simvastatin 80 mg alone and 316 mg/dL in the group randomized to ZETIA plus atorvastatin 40 or 80 mg or simvastatin 40 or 80 mg. ZETIA, administered with atorvastatin or simvastatin (40- and 80-mg statin groups, pooled), significantly reduced LDL-C (21%) compared with increasing the dose of simvastatin or atorvastatin monotherapy from 40 to 80 mg (7%). In those treated with ZETIA plus 80-mg atorvastatin or with ZETIA plus 80-mg simvastatin, LDL-C was reduced by 27%.

Homozygous Sitosterolemia (Phytosterolemia) in Adults and Pediatric Patients

A trial was conducted to assess the efficacy of ZETIA in the treatment of homozygous sitosterolemia. In this multicenter, double-blind, placebo-controlled, 8-week trial, 37 patients (age range 9 to 72 years, 65% females; 89% White, 3% Asian, 8% other races identified as Hispanic or Latino) with homozygous sitosterolemia with elevated plasma sitosterol levels (>5 mg/dL) on their current therapeutic regimen (diet, bile-acid-binding resins, statins, ileal bypass surgery and/or LDL apheresis), were randomized to receive ZETIA (n=30) or placebo (n=7). Due to decreased bioavailability of ezetimibe in patients concomitantly receiving cholestyramine [see Drug Interactions (7)], ZETIA was dosed at least 2 hours before or 4 hours after resins were administered. Excluding the one subject receiving LDL apheresis, ZETIA significantly lowered plasma sitosterol and campesterol, by 21% and 24% from baseline, respectively. In contrast, patients who received placebo had increases in sitosterol and campesterol of 4% and 3% from baseline, respectively. For patients treated with ZETIA, mean plasma levels of plant sterols were reduced progressively over the course of the trial. Reductions in sitosterol and campesterol were consistent between patients taking ZETIA concomitantly with bile acid sequestrants (n=8) and patients not on concomitant bile acid sequestrant therapy (n=21).

16 HOW SUPPLIED/STORAGE AND HANDLING

ZETIA 10 mg tablets are white to off-white, capsule-shaped, and debossed with "414" on one side and are supplied as follows:

Package Size | NDC
Bottle of 30 tablets | 78206-178-01

STORAGE AND HANDLING

Store ZETIA at room temperature between 68°F to 77°F (20°C to 25°C). Protect from moisture.

17 PATIENT COUNSELING INFORMATION

Advise the patient to read the FDA-Approved Patient Labeling (Patient Information).

Inform patients that ZETIA may cause liver enzyme elevations [see Warnings and Precautions (5.2)].

Muscle Pain

Advise patients that ZETIA may cause myopathy and rhabdomyolysis. Inform patients that the risk is also increased when taking certain types of medication and they should discuss all medication, both prescription and over the counter, with their healthcare provider. Instruct patients to promptly report any unexplained muscle pain, tenderness or weakness particularly if accompanied by malaise or fever [see Warnings and Precautions (5.3), and Drug Interactions (7)].

Pregnancy

Advise patients to inform their healthcare provider of a known or suspected pregnancy to discuss if ZETIA should be discontinued [see Use in Specific Populations (8.1)].

Breastfeeding

Advise patients who have a lipid disorder and are breastfeeding to discuss the options with their healthcare provider [see Use in Specific Populations (8.2)].

Missed Dose

Instruct patients to take ZETIA only as prescribed. If a dose is missed, it should be taken as soon as possible. Advise patients not to double their next dose.

Organon LLC, a subsidiary of
ORGANON & Co.,
Jersey City, NJ 07302, USA

For patent information: www.organon.com/our-solutions/patent/

© 2024 Organon group of companies. All rights reserved.

uspi-og0653-t-2402r003

PATIENT INFORMATION
ZETIA [zeh-TEE-uh]
(ezetimibe)
tablets, for oral use

Read this information carefully before you start taking ZETIA® and each time you get more ZETIA. There may be new information. This information does not take the place of talking with your doctor about your medical condition or your treatment. If you have any questions about ZETIA, ask your doctor. Only your doctor can determine if ZETIA is right for you.

What is ZETIA?

ZETIA is a medicine used with a cholesterol lowering diet:

- and with other cholesterol medicines called a statin, or alone (when additional cholesterol lowering treatments are not possible), to lower elevated low-density lipoprotein cholesterol (LDL-C) or bad cholesterol in adults with primary hyperlipidemia (too many fats in your blood), including heterozygous familial hypercholesterolemia (HeFH). HeFH is an inherited condition that causes high levels of bad cholesterol.
- and with a statin to lower LDL-C in adults and children 10 years of age and older with HeFH.
- and with a medicine called fenofibrate to lower elevated LDL-C in adults with mixed hyperlipidemia.
- to lower elevated sitosterol and campesterol levels in adults and in children 9 years of age and older with homozygous familial sitosterolemia (a rare inherited condition that prevents the body from getting rid of cholesterol from plants).

ZETIA is also used:

- with a statin and other cholesterol lowering treatments to lower elevated LDL-C levels in adults and patients 10 years of age and older with homozygous familial hypercholesterolemia (HoFH). HoFH is an inherited condition that causes high levels of bad cholesterol.

The safety and effectiveness of ZETIA has not been established in children:

- younger than 10 years of age with HeFH or HoFH.
- younger than 9 years of age with homozygous familial sitosterolemia.
- with other types of hyperlipemia.

Do not take ZETIA:

- if you are allergic to ezetimibe or any of the ingredients in ZETIA. See the end of this Patient Information leaflet for a complete list of ingredients in ZETIA. Stop using ZETIA and get medical help right away if you have symptoms of a serious allergic reaction including:
  - swelling of the face, tongue, or throat
  - difficulty breathing or swallowing
  - fainting or feeling dizzy
  - very fast heartbeat
  - severe skin rash, hives, and itching
  - flu-like symptoms including fever, sore throat, cough, tiredness, and joint pain
- with certain statins, fenofibrate, or other LDL-C lowering medicines if your healthcare provider has told you not to take them.

Before you take ZETIA, tell your healthcare provider about all your medical conditions, including if you:

- have liver problems. ZETIA may not be right for you.
- are pregnant or plan to become pregnant. It is not known if ZETIA will harm your unborn baby. You and your healthcare provider should decide if you will take ZETIA while you are pregnant.
- are breastfeeding. It is not known if ZETIA passes into your breast milk. You and your healthcare provider should decide the best way to feed your baby if you take ZETIA.

Tell your healthcare provider about all the medicines you take, including prescription and over-the-counter medicines, vitamins, and herbal supplements. Talk to your healthcare provider before you start taking any new medicines.

Taking ZETIA with certain other medicines may affect each other causing side effects. ZETIA may affect the way other medicines work, and other medicines may affect how ZETIA works.

Especially tell your healthcare provider if you take:

- cyclosporine (a medicine for your immune system)
- fibrates (medicine for lowering cholesterol)
- bile acid sequestrants (medicine for lowering LDL-C)

Ask your healthcare provider or pharmacist for a list of medicines if you are not sure. Know the medicines you take. Keep a list of them to show your healthcare provider and pharmacist when you get a new medicine.

How should I take ZETIA?

- Take ZETIA 1-time each day, with or without food. It may be easier to remember to take your dose if you do it at the same time every day, such as with breakfast, dinner, or at bedtime. If you also take another medicine to reduce your cholesterol, ask your healthcare provider if you can take them at the same time.
- If you miss a dose, take it as soon as you remember. If you do not remember until it is time for your next dose, skip the missed dose and go back to your regular schedule. Do not take 2 doses of ZETIA at the same time.
- While taking ZETIA, continue to follow your cholesterol-lowering diet and to exercise as your healthcare provider told you to.
- If you take a medicine called a bile acid sequestrant, take ZETIA at least 2 hours before or 4 hours after you take the bile acid sequestrant.
- Your healthcare provider may do blood tests to check your LDL-C levels as early as 4 weeks after starting treatment with ZETIA.
- In case of an overdose, get medical help or contact a live Poison Center expert right away at 1-800-222-1222. Advice is also available online at poisonhelp.org.

What are the possible side effects of ZETIA?
ZETIA may cause serious side effects including:

- increased liver enzymes. An increase in liver enzymes can happen in people taking ZETIA alone or with statins. Your healthcare provider may do blood tests to check your liver before and during treatment. Your healthcare provider may need to change or stop your treatment with ZETIA because of an increase in liver enzymes.
- muscle pain, tenderness, and weakness (myopathy). Muscle problems, including muscle breakdown (rhabdomyolysis) can happen. Tell your healthcare provider right away if:
  - you have unexplained muscle pain, tenderness, weakness, feel more tired than usual, or fever.
  - you have muscle problems that do not go away even after your healthcare provider has advised you to stop taking ZETIA. Your healthcare provider may do further tests to diagnose the cause of your muscle problems.

Your chances of getting muscle problems are higher if you are also taking statins or fibrates.
The most common side effects of ZETIA taken alone include:

- upper respiratory tract infection
- diarrhea

- joint pain
- inflammation of the sinuses

- pain in arms or legs
- feeling tired

- flu-like symptoms

The most common side effects of ZETIA taken with a statin include:

- runny nose, sore throat
- muscle aches and pains
- upper respiratory tract infection

- joint pain
- diarrhea
- back pain

- flu-like symptoms
- pain in arms or legs
- feeling tired

Tell your healthcare provider if you have any side effect that bothers you or does not go away.

These are not all the possible side effects of ZETIA.

Call your doctor for medical advice about side effects. You may report side effects to FDA at 1-800-FDA-1088.

How should I store ZETIA?

- Store ZETIA at room temperature between 68ºF to 77ºF (20ºC to 25ºC).
- Protect from moisture.

Keep ZETIA and all medicines out of the reach of children.

General information about safe and effective use of ZETIA.

Medicines are sometimes prescribed for purposes other than those listed in a Patient Information leaflet. Do not use ZETIA for a condition for which it was not prescribed. Do not give ZETIA to other people, even if they have the same symptoms you have. It may harm them.
You can ask your pharmacist or healthcare provider for information about ZETIA that is written for health professionals.

What are the ingredients in ZETIA?

Active ingredient: ezetimibe.

Inactive ingredients: croscarmellose sodium NF, lactose monohydrate NF, magnesium stearate NF, microcrystalline cellulose NF, povidone USP, and sodium lauryl sulfate NF.

Manuf. for: Organon LLC, a subsidiary of
ORGANON & Co.,
Jersey City, NJ 07302, USA
For patent information: www.organon.com/our-solutions/patent/
© 2023 Organon group of companies. All rights reserved.
For more information, go to www.organon.com/our-focus/products-list/ or call 1-844-674-3200.
usppi-og0653-t-2307r001

This Patient Information has been approved by the U.S. Food and Drug Administration.

Revised: 7/2023

PRINCIPAL DISPLAY PANEL - 10 mg Tablet Bottle Label

NDC 78206-178-01

Zetia®
(ezetimibe) tablets

10 mg

Each tablet contains 10 mg ezetimibe.

Rx only

30 Tablets